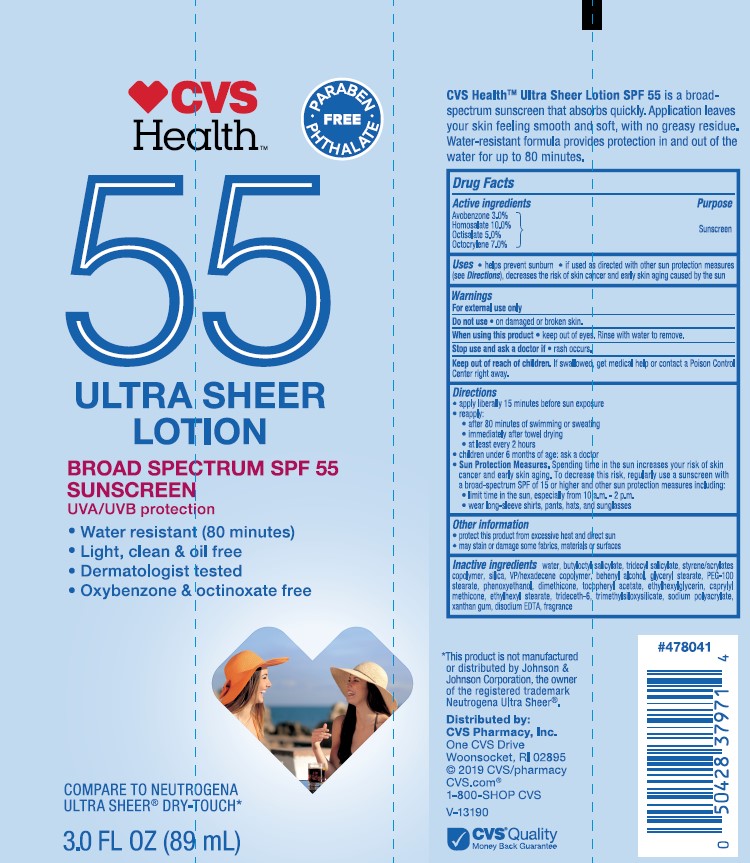 DRUG LABEL: CVS Health SPF 55 Ultra Sheer
NDC: 69842-375 | Form: LOTION
Manufacturer: CVS Pharmacy
Category: otc | Type: HUMAN OTC DRUG LABEL
Date: 20241022

ACTIVE INGREDIENTS: OCTOCRYLENE 70 mg/1 mL; OCTISALATE 50 mg/1 mL; HOMOSALATE 100 mg/1 mL; AVOBENZONE 30 mg/1 mL
INACTIVE INGREDIENTS: EDETATE DISODIUM; TRIDECETH-6; TRIMETHYLSILOXYSILICATE (M/Q 0.8-1.0); XANTHAN GUM; ETHYLHEXYL STEARATE; PHENOXYETHANOL; CAPRYLYL TRISILOXANE; ETHYLHEXYLGLYCERIN; DIMETHICONE; WATER; BUTYLOCTYL SALICYLATE; BUTYL METHACRYLATE/METHYL METHACRYLATE/METHACRYLIC ACID/STYRENE CROSSPOLYMER; SILICON DIOXIDE; VINYLPYRROLIDONE/HEXADECENE COPOLYMER; DOCOSANOL; GLYCERYL MONOSTEARATE; PEG-100 STEARATE; SODIUM POLYACRYLATE (8000 MW); TRIDECYL SALICYLATE; .ALPHA.-TOCOPHEROL ACETATE

CVS Health SPF 55 Ultra Sheer Lotion

Active ingredients

Avobenzone 3.0%, Homosalate 10.0%, Octisalate 5.0%, Octocrylene 7.0%,

Purpose

Sunscreen

Uses

- helps prevent sunburn
- if used as directed with other sun protection measures (see Directions), decreases the risk of skin cancer and early skin aging caused by the sun

Warnings

For external use only

Do not use

- on damaged or broken skin

When using this product

- keep out of eyes. Rinse with water to remove.

Stop use and ask a doctor

if rash occurs.

Keep out of reach of children.

If product is swallowed, get medical help or contact a Poison Control Center right away.

Directions

• apply liberally 15 minutes before sun exposure
reapply:
• after 80 minutes of swimming or sweating
• immediately after towel drying
• at least every 2 hours

- children under 6 months: Ask a doctor

• Sun Protection Measures. Spending time in the sun increases your risk of skin cancer and early skin aging. To decrease this risk, regularly use a sunscreen with a Broad Spectrum SPF value of 15 or higher and other sun protection measures including:
• limit time in the sun, especially from 10 a.m. - 2 p.m.
• wear long-sleeved shirts, pants, hats, and sunglasses

Inactive ingredients

water, butyloctyl salicylate, tridecyl salicylate, styrene/acrylates copolymer, silica, VP/hexadecene copolymer, behenyl alcohol, glyceryl stearate, PEG-100 stearate, phenoxyethanol, dimethicone, tocopheryl acetate, ethylhexylglycerin, caprylyl methicone, ethylhexyl stearate, trideceth-6, trimethylsiloxysilicate, sodium polyacrylate, xanthan gum, disodium EDTA, fragrance

Other information

• protect the product in this container from excessive heat and direct sun
• may stain or damage some fabrics, materials or surfaces

PACKAGE LABEL

CVS Health

ULTRA SHEER LOTION

BROAD SPECTRUM SPF 55 SUNSCREEN

3.0 FL OZ (89 mL)